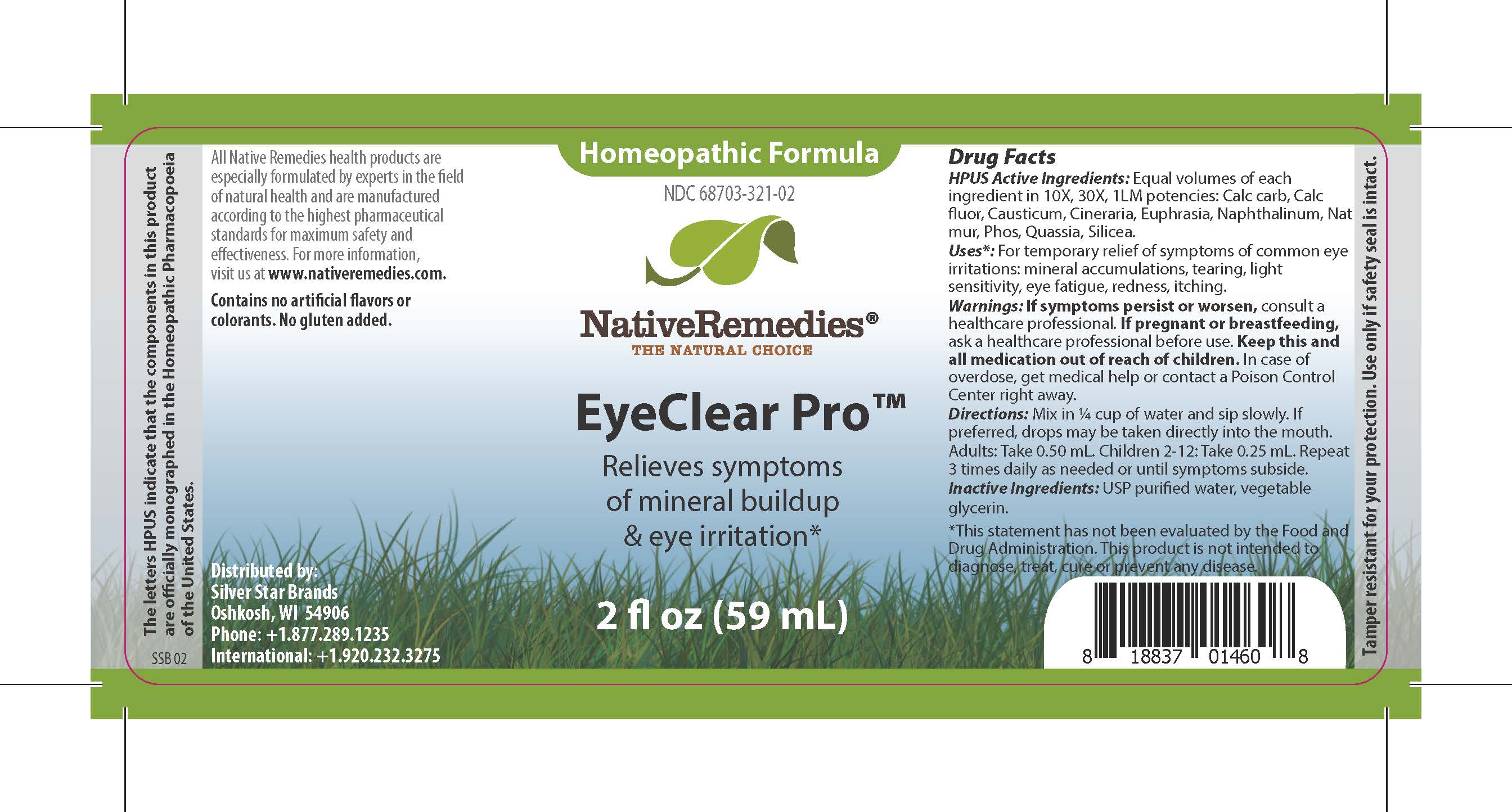 DRUG LABEL: EyeClear Pro
NDC: 68703-321 | Form: LIQUID
Manufacturer: Silver Star Brands
Category: homeopathic | Type: HUMAN OTC DRUG LABEL
Date: 20190219

ACTIVE INGREDIENTS: CAUSTICUM 10 [hp_X]/59 mL; EUPHRASIA STRICTA 10 [hp_X]/59 mL; NAPHTHALENE 10 [hp_X]/59 mL; QUASSIA AMARA WOOD 10 [hp_X]/59 mL; JACOBAEA MARITIMA 10 [hp_X]/59 mL; SILICON DIOXIDE 10 [hp_X]/59 mL; PHOSPHORUS 10 [hp_X]/59 mL; OYSTER SHELL CALCIUM CARBONATE, CRUDE 10 [hp_X]/59 mL; CALCIUM FLUORIDE 10 [hp_X]/59 mL; SODIUM CHLORIDE 10 [hp_X]/59 mL
INACTIVE INGREDIENTS: GLYCERIN; WATER

NativeRemedies® EyeClear Pro™

HPUS Active Ingredients: Equal volumes of each ingredient in 10X, 30X, 1LM potencies: Calc carb, Calc fluor, Causticum, Cineraria, Euphrasia, Naphthalinum, Nat mur, Phos, Quassia, Silicea.

The letters HPUS indicate that the components in this product are offically monographed in the Homeopathic Pharmacopoeia of the United States.

Uses*

Uses*: For temporary relief of symptoms of common eye irritations: mineral accumulations, tearing, light sensitivity, eye fatigue, redness, itching.

*This statement has not been evaluated by the Food and Drug Administration. This product is not intended to diagnose, treat, cure, or prevent any disease.

Warnings

Warnings: If symptoms persist or worsen, consult a healthcare professional. If pregnant or breastfeeding, ask a healthcare professional before use. Keep this and all medication out of reach of children. In case of overdose, get medical help or contact a Poison Control Center right away.

Directions

Directions: Mix in 1/4 cup of water and sip slowly. If preferred, drops may be taken directly into the mouth. Adults: Take 0.50 mL. Children 2-12: Take 0.25 mL. Repeat 3 times daily as needed or until symptoms subside.

OTHER SAFETY INFORMATION

Contains no artificial flavors or colorants. No gluten added.

Tamper resistant for your protection. Use only if safety seal is intact.

Inactive Ingredient

Inactive Ingredients: USP purified water, vegetable glycerin.

KEEP OUT OF REACH OF CHILDREN

Keep this and all medication out of reach of children.

PREGNANCY OR BREAST FEEDING

If pregnant or breastfeeding, ask a healthcare professional before use.

PURPOSE

Relieves symptoms of mineral buildup & eye irritation.